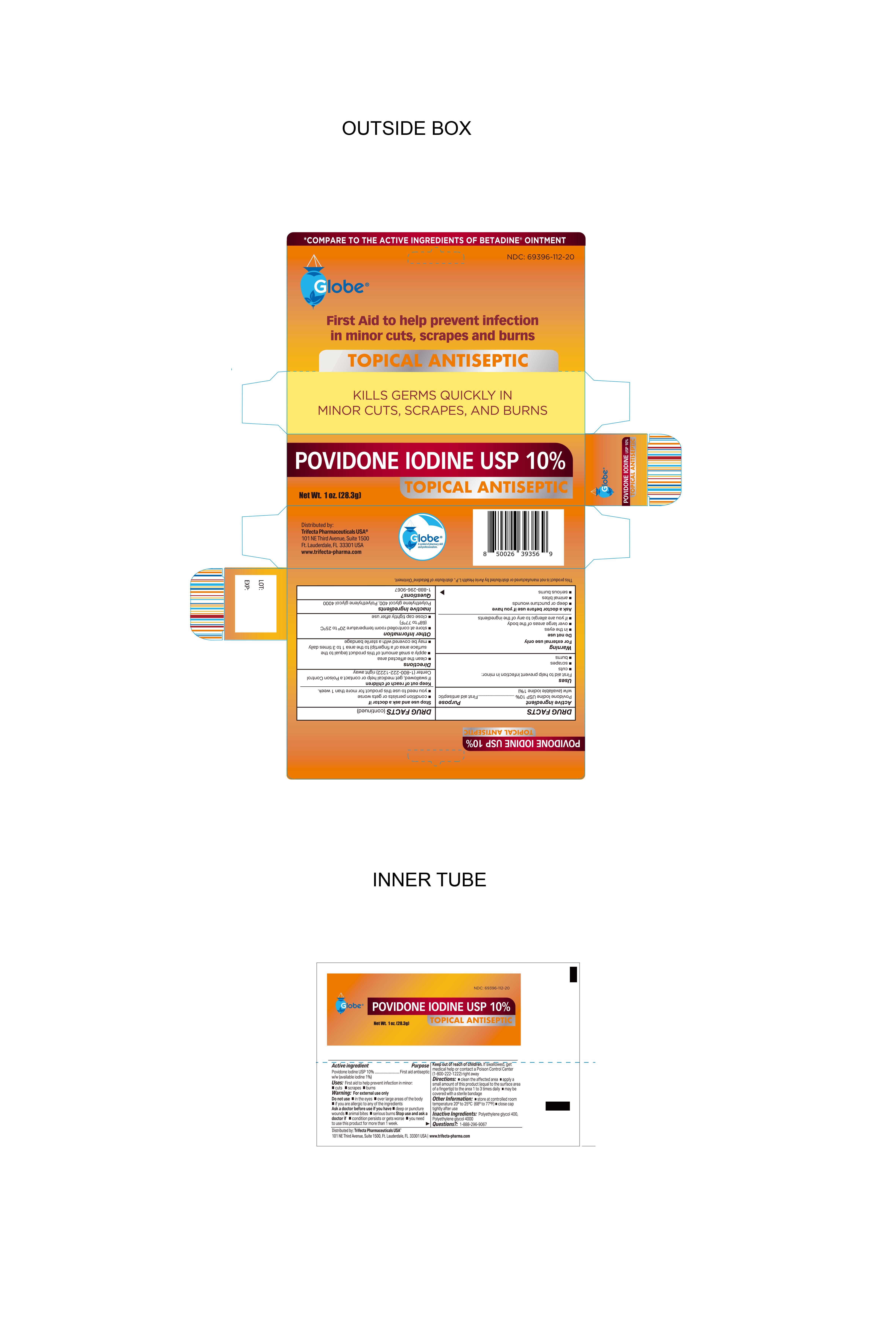 DRUG LABEL: Povidone Iodine
NDC: 69396-112 | Form: OINTMENT
Manufacturer: Trifecta Pharmaceuticals USA LLC
Category: otc | Type: HUMAN OTC DRUG LABEL
Date: 20241220

ACTIVE INGREDIENTS: POVIDONE-IODINE 100 mg/1 g
INACTIVE INGREDIENTS: POLYETHYLENE GLYCOL 4000; POLYETHYLENE GLYCOL 400

Globe Povidone Iodine USP 10%

Active Ingredient

Povidone Iodine USP 10%

w/w (available iodine 1%)

Purpose

First Aid Antiseptic

Uses

First Aid to help prevent infection in minor cuts, scrapes and burns.

Warnings

For external Use Only

Do not use

- in eyes
- over large areas of the body
- if you are allergic to any of the ingredients

Directions

- Clean the affected area
- apply a small amount of this product (equal to the surface area of a fingertip) to the area 1 to 3 times daily.
- may be covered with a sterile bandage

Ask Doctor before use if you have

- deep or puncture wounds
- animal bites
- serious burns

Inactive Ingredients

Polyethylene glycol 400, Polyethylene glycol 4000

Questions?

Call 1-888-296-9067

Stop Use and Ask a doctor if

- The condition persists or gets worse
- you need to use this product for more than 1 week

Storage Information

- Store at controlled room temperature 20º to 25ºC (68ºF to 77ºF).
- close cap tightly after use.

Keep out of reach of children

If swallowed, get medical help or contact a Poison Control Center immediately (1-800-222-1222) right away.

Questions

1-888-296-9067

Other Information

Distributed By:

Trifecta Pharmaceuticals USA®

101 NE Third Ave. Ste 1500

Ft. Lauderdale, FL. 33301 USA

www.trifecta-pharma.com